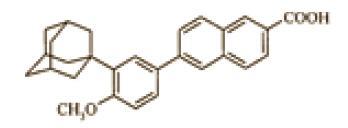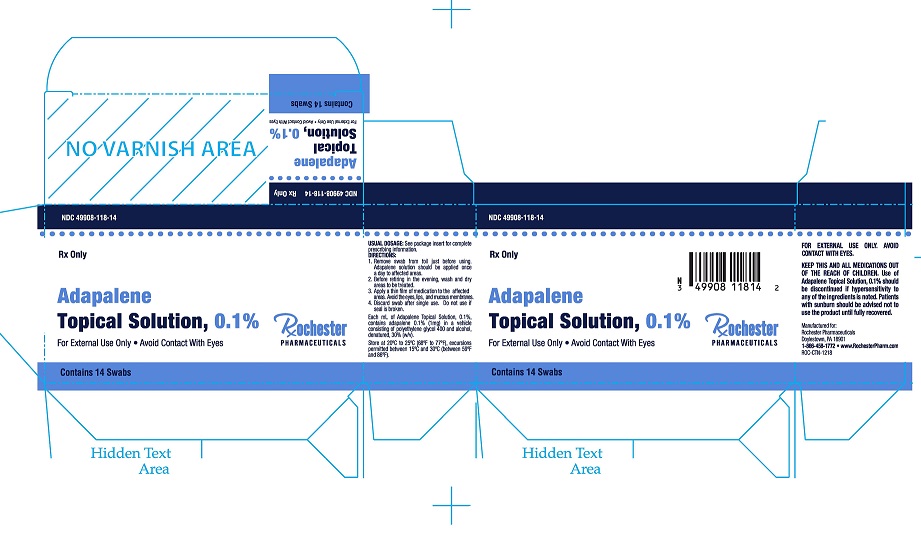 DRUG LABEL: Adapalene
NDC: 49908-118 | Form: SWAB
Manufacturer: CALL INC. (dba Rochester Pharmaceuticals)
Category: prescription | Type: HUMAN PRESCRIPTION DRUG LABEL
Date: 20250108

ACTIVE INGREDIENTS: ADAPALENE 1 mg/1 mL
INACTIVE INGREDIENTS: ALCOHOL; POLYETHYLENE GLYCOL 400

Adapalene Topical Solution, 0.1%

Rx Only

DESCRIPTION

Adapalene Topical Solution, 0.1%, containing adapalene is used for the topical treatment of acne vulgaris. Each mL of Adapalene Topical Solution, 0.1%, contains adapalene 0.1% (1 mg) in a vehicle consisting of polyethylene glycol 400 and alcohol, denatured, 30% (w/v).

The chemical name of adapalene is 6-[3-(1-adamantyl)-4-methoxyphenyl]-2-naphthoic acid. Adapalene is a white to off-white powder which is soluble in tetrahydrofuran, sparingly soluble in ethanol, and practically insoluble in water. The molecular formula is C28H28O3 and molecular weight is 412.52. Adapalene is represented by the following structural formula:

CLINICAL PHARMACOLOGY

Adapalene is a chemically stable, retinoid-like compound. Biochemical and pharmacological profile studies have demonstrated that adapalene is a modulator of cellular differentiation, keratinization, and inflammatory processes all of which represent important features in the pathology of acne vulgaris. Mechanistically, adapalene binds to specific retinoic acid nuclear receptors but does not bind to the cytosolic receptor protein. Although the exact mode of action is unknown, it is suggested that topical adapalene may normalize the differentiation of follicular epithelial cells resulting in decreased microcomedone formation.

Pharmacokinetics

Absorption of adapalene through human skin is low. Only trace amounts (< 0.25 ng/mL) of parent substance have been found in the plasma of acne patients following chronic topical application of adapalene in controlled clinical trials. Excretion appears to be primarily by the biliary route.

INDICATIONS AND USAGE

Adapalene Topical Solution, 0.1% is indicated for the topical treatment of acne vulgaris.

CONTRAINDICATIONS

Adapalene Topical Solution, 0.1% should not be administered to individuals who are hypersensitive to adapalene or any of the components in the vehicle solution.

WARNINGS

Use of Adapalene Topical Solution, 0.1% should be discontinued if hypersensitivity to any of the ingredients is noted. Patients with sunburn should be advised not to use the product until fully recovered.

PRECAUTIONS

General

If a reaction suggesting sensitivity or chemical irritation occurs, use of the medication should be discontinued. Exposure to sunlight, including sunlamps, should be minimized during the use of adapalene. Patients who normally experience high levels of sun exposure, and those with inherent sensitivity to sun, should be warned to exercise caution. Use of sunscreen products and protective clothing over treated areas is recommended when exposure cannot be avoided. Weather extremes, such as wind or cold, also may be irritating to patients under treatment with adapalene.

Avoid contact with the eyes, lips, angles of the nose, and mucous membranes. The product should not be applied to cuts, abrasions, eczematous skin, or sunburned skin.

Certain cutaneous signs and symptoms such as erythema, dryness, scaling, burning, or pruritus may be experienced during treatment. These are most likely to occur during the first two to four weeks and will usually lessen with continued use of the medication. Depending upon the severity of adverse events, patients should be instructed to reduce the frequency of application or discontinue use.

Drug Interactions

As Adapalene Topical Solution, 0.1% has the potential to produce local irritation in some patients, concomitant use of other potentially irritating topical products (medicated or abrasive soaps and cleansers, soaps and cosmetics that have a strong drying effect, and products with high concentrations of alcohols, astringents, spices or lime) should be approached with caution. Particular caution should be exercised in using preparations containing sulfur, resorcinol, or salicylic acid in combination with Adapalene Topical Solution, 0.1%. If these preparations have been used, it is advisable not to start therapy with Adapalene Topical Solution, 0.1% until the effects of such preparations in the skin have subsided.

Carcinogenesis, Mutagenesis, Impairment of Fertility

Carcinogenicity studies with adapalene have been conducted in mice at topical doses of 0.3, 0.9, and 2.6 mg/kg/day and in rats at oral doses of 0.15, 0.5, and 1.5 mg/kg/day, approximately 4-75 times the maximal daily human topical dose. In the oral study, positive linear trends were observed in the incidence of follicular cell adenomas and carcinomas in the thyroid glands of female rats, and in the incidence of benign and malignant pheochromocytomas in the adrenal medullas of male rats.

No photocarcinogenicity studies were conducted. Animal studies have shown an increased tumorigenic risk with the use of pharmacologically similar drugs (e.g., retinoids) when exposed to UV irradiation in the laboratory or to sunlight. Although the significance of these studies to humans is not clear, patients should be advised to avoid or minimize exposure to either sunlight or artificial UV irradiation sources.

In a series of in vivo and in vitro studies, adapalene did not exhibit mutagenic or genotoxic activities.

Pregnancy

Teratogenic effects

Pregnancy Category C

No teratogenic effects were seen in rats at oral doses of adapalene 0.15 to 5.0 mg/kg/day, up to 120 times the maximal daily human topical dose. Cutaneous route teratology studies conducted in rats and rabbits at doses of 0.6, 2.0, and 6.0 mg/kg/day, up to 150 times the maximal daily human topical dose exhibited no fetotoxicity and only minimal increases in supernumerary ribs in rats. There are no adequate well-controlled studies in pregnant women. Adapalene should be used during pregnancy only if the potential benefit justifies the potential risk to the fetus.

Nursing Mothers

It is not known whether this drug is excreted in human milk. Because many drugs are excreted in human milk, caution should be exercised when Adapalene Topical Solution, 0.1% is administered to a nursing woman.

Pediatric Use

Safety and effectiveness in pediatric patients below the age of 12 have not been established.

ADVERSE REACTIONS

Some adverse effects such as erythema, scaling, dryness, pruritus, and burning will occur in 30-60% of patients. Pruritus or burning immediately after application also occurs in approximately 30% of patients. The following additional adverse experiences were reported in approximately 1% or less of patients: skin irritation, burning/stinging, erythema, sunburn, and acne flares. These are most commonly seen during the first month of therapy and decrease in frequency and severity thereafter. All adverse effects with the use of adapalene solution during clinical trials were reversible upon discontinuation of therapy.

To report SUSPECTED ADVERSE REACTIONS, contact Rochester Pharmaceuticals at 1 -866-458-1772 or FDA at 1-800-FDA-1088 or www.fda.gov/medwatch.

OVERDOSAGE

Adapalene Topical Solution, 0.1% is intended for cutaneous use only. If the medication is applied excessively, no more rapid or better results will be obtained and marked redness, peeling, or discomfort may occur. The acute oral toxicity of Adapalene Topical Solution, 0.1% in mice and rats is greater than 10 mL/kg. Chronic ingestion of the drug may lead to the same side effects as those associated with excessive oral intake of Vitamin A.

DOSAGE AND ADMINISTRATION

1. Remove swab from foil just before using. Adapalene solution should be applied once a day to affected areas.
2. Before retiring in the evening, wash and dry areas to be treated.
3. Apply a thin film of medication to the affected areas. Avoid the eyes, lips, and mucous membranes.
4. Discard swab after single use. Do not use if seal is broken.

During the early weeks of therapy, an apparent exacerbation of acne may occur. This is due to the action of the medication on previously unseen lesions and should not be considered a reason to discontinue therapy. Therapeutic results should be noticed after eight to twelve weeks of treatment.

HOW SUPPLIED

Adapalene Topical Solution, 0.1% is supplied in the following size:
14-count unit-of-use 1.2g swab - NDC 49908-118-14

Storage

Store at 20°C to 25°C (68°F to 77°F); excursions permitted between 15°C and 30°C (59°F and 86°F).

CAUTION

Federal law prohibits dispensing without prescription.

Distributed by:
Rochester Pharmaceuticals
Doylestown, PA 18901

ROC-PI-1218

PRINCIPAL DISPLAY PANEL - 14 Swab Carton

NDC 49908-118-14

Rx Only

Adapalene
Topical Solution, 0.1%

For External Use Only • Avoid Contact With Eyes

Rochester Pharmaceuticals

Contains 14 Swabs